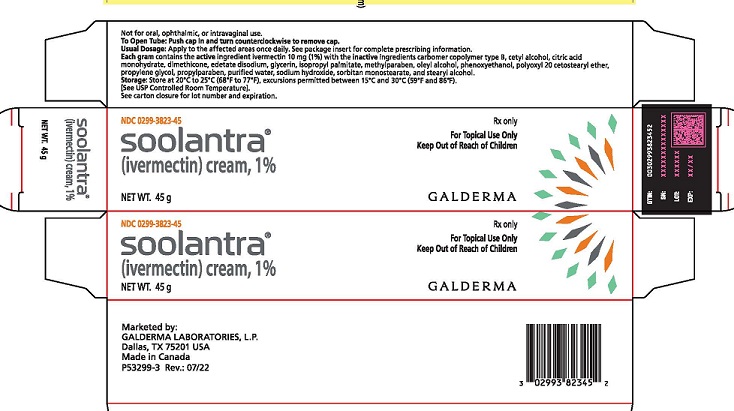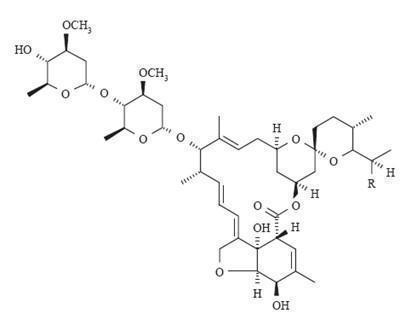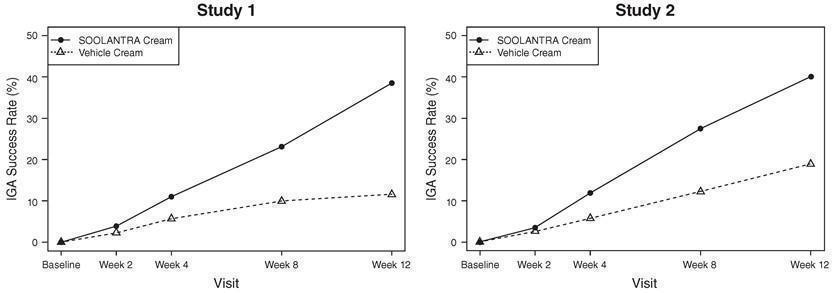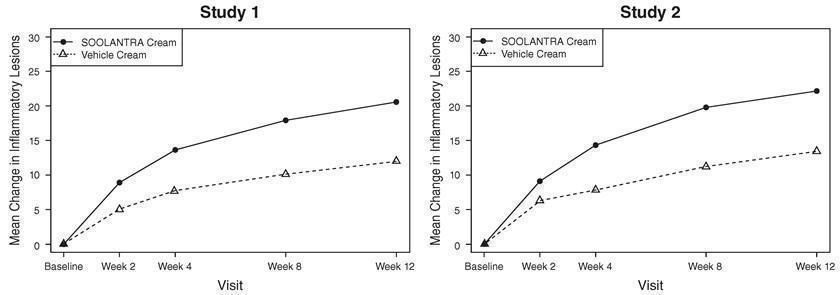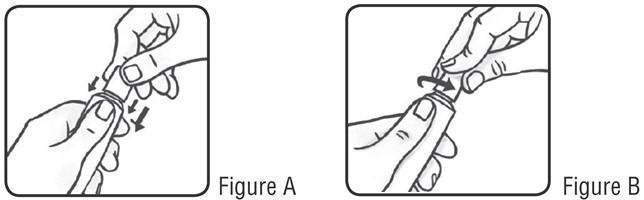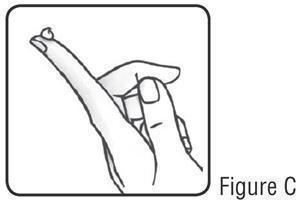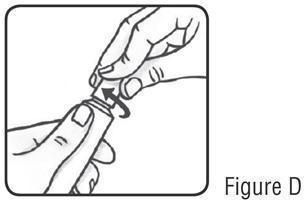 DRUG LABEL: SOOLANTRA
NDC: 0299-3823 | Form: CREAM
Manufacturer: Galderma Laboratories, L.P.
Category: prescription | Type: HUMAN PRESCRIPTION DRUG LABEL
Date: 20241024

ACTIVE INGREDIENTS: IVERMECTIN 10 mg/1 g
INACTIVE INGREDIENTS: CARBOMER COPOLYMER TYPE B (ALLYL PENTAERYTHRITOL CROSSLINKED); CETYL ALCOHOL; CITRIC ACID MONOHYDRATE; DIMETHICONE; EDETATE DISODIUM; GLYCERIN; ISOPROPYL PALMITATE; METHYLPARABEN; OLEYL ALCOHOL; PHENOXYETHANOL; POLYOXYL 20 CETOSTEARYL ETHER; PROPYLENE GLYCOL; PROPYLPARABEN; WATER; SODIUM HYDROXIDE; SORBITAN MONOSTEARATE; STEARYL ALCOHOL

HIGHLIGHTS OF PRESCRIBING INFORMATION

These highlights do not include all the information needed to use SOOLANTRA Cream safely and effectively. See full prescribing information for SOOLANTRA Cream.
SOOLANTRA®(ivermectin) cream, 1%, for topical use
Initial U.S. Approval: 1996

1 INDICATIONS AND USAGE

SOOLANTRA cream is indicated for the treatment of inflammatory lesions of rosacea. (1)

2 DOSAGE AND ADMINISTRATION

- Apply to the affected areas once daily. (2)
- Not for oral, ophthalmic or intravaginal use. (2)

3 DOSAGE FORMS AND STRENGTHS

Cream, 1% (3)

4 CONTRAINDICATIONS

None. (4)

6 ADVERSE REACTIONS

In controlled clinical trials with SOOLANTRA cream the most common adverse reactions (incidence ≤ 1 %) included skin burning sensation and skin irritation. (6.1)

To report SUSPECTED ADVERSE REACTIONS, contact Galderma Laboratories, L.P. at 1-866-735-4137 or FDA at 1-800-FDA-1088 or www.fda.gov/medwatch.

FULL PRESCRIBING INFORMATION

1 INDICATIONS AND USAGE

SOOLANTRA cream is indicated for the treatment of inflammatory lesions of rosacea.

2 DOSAGE AND ADMINISTRATION

Apply to the affected areas of the face once daily. Use a pea-size amount for each area of the face (forehead, chin, nose, each cheek) that is affected. Spread as a thin layer, avoiding the eyes and lips.
SOOLANTRA cream is not for oral, ophthalmic, or intravaginal use.

3 DOSAGE FORMS AND STRENGTHS

Cream, 1%.
Each gram of SOOLANTRA cream contains 10 mg of ivermectin in a white to pale yellow cream base. SOOLANTRA cream is supplied in tubes of 30 g, 45 g and 60 g.

4 CONTRAINDICATIONS

None.

6 ADVERSE REACTIONS

6.1 Clinical Trials Experience

Because clinical trials are conducted under widely varying conditions, adverse reaction rates observed in the clinical trials of a drug cannot be directly compared to rates in the clinical trials of another drug and may not reflect the rates observed in practice.
During clinical trials, 2047 subjects with inflammatory lesions of rosacea received SOOLANTRA cream once daily. A total of 1555 subjects were treated once daily for more than 12 weeks, and 519 for approximately one year.
Adverse reactions, reported in ≤ 1% of subjects treated with SOOLANTRA cream for at least 3 months in vehicle-controlled clinical trials, included skin burning sensation and skin irritation.

6.2 Postmarketing Experience

Because adverse reactions are reported voluntarily from a population of uncertain size, it is not always possible to reliably estimate their frequency or establish a causal relationship to drug exposure.
Local adverse reactions: contact dermatitis and allergic dermatitis.

7 DRUG INTERACTIONS

In vitro studies have shown that SOOLANTRA cream, at therapeutic concentrations, neither inhibits nor induces cytochrome P450 (CYP450) enzymes.

8 USE IN SPECIFIC POPULATIONS

8.1 Pregnancy

Risk Summary
The available data on the use of ivermectin, including SOOLANTRA cream, in pregnant women are insufficient to establish a drug- associated risk of major birth defects, miscarriage, or adverse maternal or fetal outcomes.
In animal reproduction studies, ivermectin induced adverse developmental outcomes when orally administered to pregnant rats and rabbits during the period of organogenesis at doses 1909 or 354 times the maximum recommended human dose (MRHD), respectively. These orally administered doses were maternally toxic to pregnant rats and rabbits. In a pre-and postnatal developmental study in rats, neonatal toxicity and adverse effects on behavioral development were observed when ivermectin was orally administered to pregnant females during gestation and lactation (see Data).
The background risk of major birth defects and miscarriage for the indicated population is unknown. All pregnancies have a background risk of birth defect, loss, or other adverse outcomes. In the U.S. general population, the estimated background risk of major birth defects and miscarriage in clinically recognized pregnancies is 2 to 4% and 15 to 20%, respectively.

Data
Human Data
No adequate and well-controlled trials of Soolantra cream have been conducted in pregnant women. Retrospective observational studies evaluated pregnancy outcomes in over 700 women in various stages of pregnancy who received oral ivermectin for the treatment of soil-transmitted helminths in rural Africa. In an additional, randomized open-label trial, 397 pregnant women in their second trimester received a single dose of oral ivermectin, or ivermectin plus albendazole, for soil-transmitted helminths. When compared with a pregnant, untreated population, no differences in pregnancy outcomes were observed between the treated and untreated populations. These studies cannot definitively establish or exclude any drug-associated risk during pregnancy, because either the timing of administration during gestation was not accurately ascertained or the administration occurred only during the second trimester.

Animal Data
Systemic embryofetal development studies were conducted in rats and rabbits. Oral doses of 1.5, 4, and 12mg/kg/day ivermectin were administered during the period of organogenesis to pregnant female rats. Maternal death occurred at 12 mg/kg/day [1909 times the MRHD based on area under the curve (AUC) comparison]. Cleft palate occurred in the fetuses from the 12 mg/kg/day (1909 times the MRHD based on AUC comparison) group. No treatment related embryofetal toxicity or malformations were noted at 4 mg/kg/day (708 times the MRHD based on AUC comparison). Oral doses of 0.5, 1.5, 2.5, 3.5 and 4.5 mg/kg/day ivermectin were administered during the period of organogenesis to pregnant female rabbits. Maternal death occurred at doses ≥ 2.5 mg/kg/day (72 times the MRHD based on AUC comparison). Carpal flexure occurred in the fetuses from the 4.5 mg/kg/day (354 times the MRHD based on AUC comparison) group. Fetal weight decrease was noted at 3.5 mg/kg/day (146 times the MRHD based on AUC comparison). No treatment related embryofetal toxicity or malformations were noted at 2.5 mg/kg/day (72 times the MRHD based on AUC comparison).
A pre- and postnatal development study was conducted in rats. Oral doses of 1, 2 and 4 mg/kg/day ivermectin were administered to pregnant female rats during gestational days 6-20 and lactation days 2-20. Neonatal death occurred at doses ≥ 2 mg/kg/day. Behavior development of newborn rats was adversely affected at all doses.

8.2 Lactation

Risk Summary
The presence of ivermectin in human milk following topical administration of ivermectin has not been evaluated. There are no data available regarding the effects of ivermectin on milk production. Published literature suggests that ivermectin was detectable in human milk in 4 lactating women after a single 150 mcg/kg oral dose of ivermectin. However, there is insufficient information from this report to determine the effects of ivermectin on the breastfed infant. The developmental and health benefits of breastfeeding should be considered along with the mother’s clinical need for Soolantra cream and any potential adverse effects on the breastfed infant from Soolantra cream or from the underlying maternal conditions.

8.4 Pediatric Use

Safety and effectiveness of SOOLANTRA cream in pediatric patients have not been established.

8.5 Geriatric Use

Of the 1371 subjects in the two pivotal clinical studies of SOOLANTRA cream, 170 (12.4%) were 65 and over, while 37 (2.7%) were 75 and over. No overall differences in safety or effectiveness were observed between these subjects and younger subjects, and other reported clinical experience has not identified differences in responses between the elderly and younger patients, but greater sensitivity of some older individuals cannot be ruled out.

10 OVERDOSAGE

In accidental or significant exposure to unknown quantities of veterinary formulations of ivermectin in humans, either by ingestion, inhalation, injection, or exposure to body surfaces, the following adverse effects have been reported most frequently: rash, edema, headache, dizziness, asthenia, nausea, vomiting, and diarrhea. Other adverse effects that have been reported include: seizure, ataxia, dyspnea, abdominal pain, paresthesia, urticaria, and contact dermatitis.

In case of accidental ingestion, supportive therapy, if indicated, should include parenteral fluids and electrolytes, respiratory support (oxygen and mechanical ventilation if necessary) and pressor agents if clinically significant hypotension is present. Induction of emesis and/or gastric lavage as soon as possible, followed by purgatives and other routine anti-poison measures, may be indicated if needed to prevent absorption of ingested material.

11 DESCRIPTION

SOOLANTRA (ivermectin) cream, 1% is a white to pale yellow hydrophilic cream intended for topical use. Each gram of SOOLANTRA cream contains 10 mg of ivermectin.

Ivermectin is a semi-synthetic derivative isolated from the fermentation of Streptomyces avermitilis that belongs to the avermectin family of macrocyclic lactones.

Ivermectin is a mixture containing not less than 95.0% and not more than 102.0% of 5-O-demethyl-22,23-dihydroavermectin A1aplus 5-O-demethyl-25-de(1-methylpropyl)-25-(1-methylethyl)-22,23-dihydroavermectin A1a, generally referred to as 22,23-dihydroavermectin B1aand B1bor H2B1aand H2B1b, respectively; and the ratio (calculated by area percentage) of component H2B1a/(H2B1a+ H2B1b) is not less than 90.0%.
The respective empirical formulas of H2B1aand H2B1bare C48H74O14and C47H72O14with molecular weights of 875.10 and 861.07 respectively.

The structural formulas are:

Component H2B1a: R = C2H5, Component H2B1b: R = CH3.

SOOLANTRA cream contains the following inactive ingredients: carbomer copolymer type B, cetyl alcohol, citric acid monohydrate, dimethicone, edetate disodium, glycerin, isopropyl palmitate, methylparaben, oleyl alcohol, phenoxyethanol, polyoxyl 20 cetostearyl ether, propylene glycol, propylparaben, purified water, sodium hydroxide, sorbitan monostearate, and stearyl alcohol.

12 CLINICAL PHARMACOLOGY

12.1 Mechanism of Action

The mechanism of action of SOOLANTRA cream in treating rosacea lesions is unknown.

12.2 Pharmacodynamics

Cardiac Electrophysiology
At therapeutic doses, SOOLANTRA cream is not expected to prolong QTc interval.

12.3 Pharmacokinetics

Absorption
The absorption of ivermectin from SOOLANTRA cream was evaluated in a clinical trial in 15 adult male and female subjects with severe papulopustular rosacea applying 1 g SOOLANTRA cream, 1% once daily. At steady state (after 2 weeks of treatment), the highest mean ± standard deviation plasma concentrations of ivermectin peaked (Tmax) at 10 ± 8 hours post dose, the maximum concentration (Cmax) was 2.10 ± 1.04 ng/mL (range: 0.69 - 4.02 ng/mL) and the area under the concentration curve (AUC0-24hr) was 36.14 ± 15.56 ng.hr/mL (range: 13.69-75.16 ng.hr/mL). In addition, systemic exposure assessment in longer treatment duration (Phase 3 studies) showed that there was no plasma accumulation of ivermectin over the 52-week treatment period.

Distribution
An in vitro study demonstrated that ivermectin is greater than 99% bound to plasma proteins and is bound primarily to human serum albumin. No significant binding of ivermectin to erythrocytes was observed.

Metabolism
In vitro studies using human hepatic microsomes and recombinant CYP450 enzymes have shown that ivermectin is primarily metabolized by CYP3A4. In vitro studies show that ivermectin at therapeutic concentrations does not inhibit the CYP450 isoenzymes 1A2, 2A6, 2B6, 2C8, 2C9, 2C19, 2D6, 2E1, 3A4 or 4A11, or induce 1A2, 2B6, 2C9 or 3A4.

Excretion
The apparent terminal half-life averaged 6.5 days (mean ± standard deviation: 155± 40 hours, range 92-238 hours) in patients receiving a once daily cutaneous application of SOOLANTRA cream for 28 days.

13 NONCLINICAL TOXICOLOGY

13.1 Carcinogenesis, Mutagenesis, Impairment of Fertility

In a 2-year dermal mouse carcinogenicity study, ivermectin was administered to CD-1 mice at topical doses of 1, 3, and 10 mg/kg/day (0.1%, 0.3% and 1% ivermectin cream applied at 2 ml/kg/day). No drug-related tumors were noted in this study up to the highest dose evaluated in this study of 10 mg/kg/day (747 times the MRHD based on AUC comparison).

In a 2-year oral rat carcinogenicity study, ivermectin was administered to Wistar rats at gavage doses of 1, 3, and 9 mg/kg/day. A statistically significant increase in the incidence of hepatocellular adenoma was noted in males treated with 9 mg/kg/day (1766 times the MRHD based on AUC comparison) ivermectin. The clinical relevance of this finding is unknown. No drug-related tumors were noted in females up to the highest dose evaluated in this study of 9 mg/kg/day (1959 times the MRHD based on AUC comparison). No drug-related tumors were noted in males at doses ≤ 3 mg/kg/day (599 times the MRHD based on AUC comparison).

Ivermectin revealed no evidence of genotoxic potential based on the results of two in vitro genotoxicity tests (the Ames test and the L5178Y/TK+/-mouse lymphoma assay) and one in vivo genotoxicity test (rat micronucleus assay).

In a fertility study, oral doses of 0.1, 1 and 9 mg/kg/day ivermectin were administered to male and female rats. Mortality occurred at 9 mg/kg/day (1027 times the MRHD based on AUC comparison). The precoital period was generally prolonged at 9 mg/kg/day. No treatment-related effects on fertility or mating performance were noted at doses ≤ 1 mg/kg/day (68 times the MRHD based on AUC comparison).

14 CLINICAL STUDIES

SOOLANTRA cream applied once daily at bedtime was evaluated in the treatment of inflammatory lesions of rosacea in two randomized, double-blind, vehicle controlled clinical trials, which were identical in design. The trials were conducted in 1371 subjects aged 18 years and older who were treated once daily for 12 weeks with either SOOLANTRA cream or vehicle cream.

Overall, 96% of subjects were Caucasian and 67% were female. Using the 5-point Investigator Global Assessment (IGA) scale (0=clear, 1=almost clear, 2=mild, 3=moderate, 4=severe), 79% of subjects were scored as moderate (IGA=3) and 21% scored as severe (IGA= 4) at baseline.

The co-primary efficacy endpoints in both pivotal trials were the success rate based on the IGA outcome (percentage of subjects “clear” and “almost clear”) and absolute change from baseline in inflammatory lesion counts at Week 12. Table 1 presents the co-primary efficacy results at Week 12. SOOLANTRA cream was more effective than vehicle cream on the co-primary efficacy endpoints starting from 4 weeks of treatment in both studies, see Figures 1 through 4.

Table 1: Co-Primary Efficacy Results at Week 12
 | Study 1 | Study 2
 | SOOLANTRA Vehicle Cream (N=451) Cream (N=232) | SOOLANTRA Vehicle Cream (N=459) Cream (N=229)
Investigator Global Assessment: Number (%) of Subjects Clear or Almost Clear | 173 (38.4%) 27 (11.6%) | 184 (40.1%) 43 (18.8%)
Inflammatory Lesion Counts: Mean Absolute (%) Change from Baseline | 20.5 (64.9%) 12.0 (41.6%) | 22.2 (65.7%) 13.4 (43.4%)

Figures 1 and 2: IGA Success Rates Over Time

Figures 3 and 4: Mean Absolute Change in Inflammatory Lesion Counts from Baseline Over Time

16 HOW SUPPLIED/STORAGE AND HANDLING

SOOLANTRA (ivermectin) cream, 1% is a white to pale yellow cream, supplied in a laminated tube with a child resistant cap in the following sizes:
30 gram NDC0299-3823-30
45 gram NDC0299-3823-45
60 gram NDC0299-3823-60

Storage
Store at 20°C to 25°C (68°F to 77°F), excursions permitted between 15°C and 30°C (59°F and 86°F) [See USP Controlled Room Temperature].

17 PATIENT COUNSELING INFORMATION

Advise the patient to read the FDA-approved patient labeling (Instructions for Use).

Patients using SOOLANTRA cream should receive the following instruction:

Keep out of reach of children.

Marketed by:
GALDERMA LABORATORIES, L.P.
Dallas, Texas 75201 USA

Made in Canada.

P52476-3

Instructions for Use

SOOLANTRA® (SOO-LAWN-TRAH)
(ivermectin) cream

Important: SOOLANTRA cream is for use on the skin only (topical use). Do not use SOOLANTRA cream in your eyes, mouth or vagina.

Read and follow the steps below so that you use SOOLANTRA cream correctly:

1. Open the tube of SOOLANTRA cream by gently pressing down on the child resistant cap and twist in the direction of the arrow (counterclockwise) as shown below. See Figures A and B. To avoid spilling, do not squeeze the tube while opening or closing.

2. To apply SOOLANTRA cream to your face, squeeze a pea-sized amount of SOOLANTRA cream from the tube onto your fingertip. See Figure C.

3. Apply SOOLANTRA to the affected areas of your face 1 time a day. Use a pea-sized amount of SOOLANTRA cream for each area of your face (forehead, chin, nose, each cheek) that is affected. Spread the cream smoothly and evenly in a thin layer. Avoid contact with your eyes and lips.

4. To close SOOLANTRA cream, gently press down on the child resistant cap and twist to the right (clockwise). See Figure D.

How should I store SOOLANTRA cream?

- Store SOOLANTRA cream at room temperature between 68°F to 77°F (20°C to 25°C).

Keep SOOLANTRA cream and all medicines out of the reach of children.

Marketed by: GALDERMA LABORATORIES, L.P. Dallas, TX 75201 USA
P52476-3
Made in Canada.
This Instructions for Use has been approved by the U.S. Food and Drug Administration. Revised:10/2022

PATIENT INFORMATION

SOOLANTRA® (SOO-LAWN-TRAH)
(ivermectin) cream

Important: SOOLANTRA cream is for use on the skin only (topical use).Do not use SOOLANTRA cream in your mouth, eyes, or vagina.

What is SOOLANTRA cream?
SOOLANTRA cream is a prescription medicine used on the skin (topical) to treat pimples and bumps (inflammatory lesions) caused by a condition called rosacea.
It is not known if SOOLANTRA cream is safe and effective in children.

Before using SOOLANTRA cream, tell your healthcare provider about all your medical conditions, including if you:

- are pregnant or plan to become pregnant. It is not known if SOOLANTRA cream will harm your unborn baby.
- are breastfeeding or plan to breastfeed. It is not known if SOOLANTRA cream passes into your breast milk. Talk to your healthcare provider about the best way to feed your baby if you use SOOLANTRA cream.

Tell your healthcare provider about all of the medicines you take, including prescription and over-the-counter medicines, vitamins, and herbal supplements.

How should I use SOOLANTRA cream?
See the detailed “Instructions for Use” that comes with SOOLANTRA cream for information on how to apply SOOLANTRA cream.

- Use SOOLANTRA cream exactly as your healthcare provider tells you to.
- Apply SOOLANTRA cream to the affected areas of your face 1 time a day.
- Avoid contact with your eyes and lips
- if SOOLANTRA cream is accidentally swallowed (ingested), call your healthcare provider or go to the nearest hospital emergency room right away.

What are the possible side effects of SOOLANTRA cream?
The most common side effects of SOOLANTRA cream includeskin burning sensation and skin irritation. These are not all of the possible side effects of SOOLANTRA cream.
Call your doctor for medical advice about side effects. You may report side effects to FDA at 1-800-FDA-1088.
You may also report side effects to Galderma Laboratories, L.P. at 1-866-735-4137.

How should I store SOOLANTRA cream?

- Store SOOLANTRA cream at room temperature between 68°F to 77°F (20°C to 25°C).

Keep SOOLANTRA cream and all medicines out of the reach of children.

General information about the safe and effective use of SOOLANTRA cream.
Medicines are sometimes prescribed for purposes other than those listed in a Patient Information leaflet. Do not use SOOLANTRA cream for a condition for which it was not prescribed. Do not give SOOLANTRA cream to other people, even if they have the same symptoms that you have. It may harm them. You can ask your pharmacist or healthcare provider for information about SOOLANTRA cream that is written for health professionals.

What are the ingredients in SOOLANTRA cream?
Active ingredient:ivermectin
Inactive ingredients:carbomer copolymer type B, cetyl alcohol, citric acid monohydrate, dimethicone, edetate disodium, glycerin, isopropyl palmitate, methylparaben, oleyl alcohol, phenoxyethanol, polyoxyl 20 cetostearyl ether, propylene glycol, propylparaben, purified water, sodium hydroxide, sorbitan monostearate, and stearyl alcohol.

Marketed by: Galderma Laboratories, L.P., Dallas, Texas 75201 USA
P52476-3
Made in Canada
For more information about SOOLANTRA cream, call 1-866-735-4137.

This Patient Information has been approved by the U.S. Food and Drug Administration. Issued: 10/2022

Package Label - 45 g

NDC 0299-3823-45

soolantra®

(ivermectin) cream, 1%

NET WT. 45 g

Rx only

For Topical Use Only

Keep Out of Reach of Children

GALDERMA

Marketed by:
GALDERMA LABORATORIES, L.P.
Dallas, TX 75201 USA
Made in Canada
P53299-3 Rev: 07/22

Not for oral, ophthalmic, or intravaginal use.
To Open Tube: Push cap in and turn counterclockwise to remove cap.
Usual Dosage: Apply to the affected areas once daily. See package insert for complete prescribing information.
Each gram contains the active ingredient ivermectin 10 mg (1%) with the inactive ingredients carbomer copolymer type B, cetyl alcohol, citric acid monohydrate, dimethicone, edetate disodium, glycerin, isopropyl palmitate, methylparaben, oleyl alcohol, phenoxyethanol, polyoxyl 20 cetostearyl ether, propylene glycol, propylparaben, purified water, sodium hydroxide, sorbitan monostearate, and stearyl alcohol.
Storage: Store at 20°C to 25°C (68°F to 77°F), excursions permitted between 15°C and 30°C (59°F and 86°F).
(See USP Controlled Room Temperature).
See carton closure for lot number and expiration.